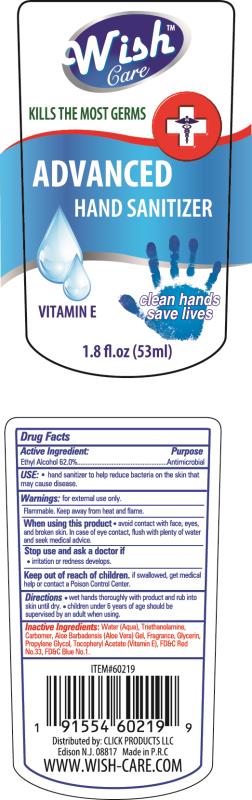 DRUG LABEL: Advanced Hand Sanitizer
NDC: 71611-011 | Form: GEL
Manufacturer: Click Products LLC
Category: otc | Type: HUMAN OTC DRUG LABEL
Date: 20200409

ACTIVE INGREDIENTS: ALCOHOL 62 g/53 mL
INACTIVE INGREDIENTS: WATER; CARBOXYMETHYL FRAGMENT; ALOE VERA FLOWER; PPG-1-PEG-9 LAURYL GLYCOL ETHER; SODIUM HYDROXIDE

Advanced Hand Sanitizer - Vitamin E

Active Ingredient

Ethyl Alcohol...........62%

PURPOSE

Antimicrobial

Keep out of reach of children.

Warnings

- for external use only-hands.
- keep out of eyes. avoid contact with broken skin.
- stop use and ask a Doctor if irritation or redness develops.
- do not inhale or ingest. if swallowed, get medical help or contact a poison control center right away.

Directions

- Rub a dime sized drop into hands.
- For children under 6 use under adult supervision.

Inactive Ingredients

water (aqua/eau), glycerin, coceth-7, PPG-1-PEG-9 lauryl glycol ether, carbomer, hydrogenated castor oil, fragrance (parfum).

May Contain

Red 40 (CI 16035), Red 33 (CI 17200), Blue 1 (CI 42090)

INDICATIONS AND USAGE

Hand Sanitizer